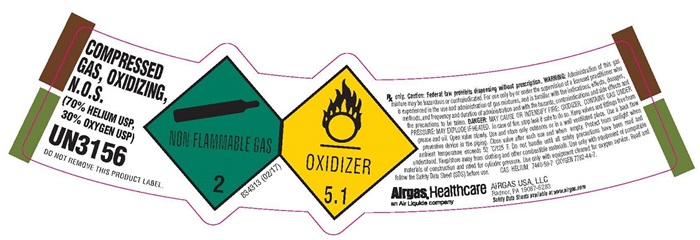 DRUG LABEL: Helium Oxygen mixture
NDC: 11054-032 | Form: GAS
Manufacturer: Airgas Usa, LLC
Category: prescription | Type: HUMAN PRESCRIPTION DRUG LABEL
Date: 20241001

ACTIVE INGREDIENTS: HELIUM 700 mL/1 L; OXYGEN 300 mL/1 L

Helium Oxygen Mixture 032

Helium/Oxygen Mix

UN1956

COMPRESSED GASES, N.O.S.

(HELIUM, OXYGEN)

Components:

% HELIUM USP CAS: 7740-59-7

% OXYGEN USP CAS: 7782-44-7

LOT NUMBER

NET CONTENTS

CAUTION! HIGH-PRESSURE GAS. MAY ACCELERTE COMBUSTION CONCENTRATIONS BELOW 19.5% OXYGEN CAN CAUSE SUFFOCATION. MAY CAUSE DIZZINESS AND DROWSINESS.

Keep oil, grease and combustibles away. Keep away from heat, sparks, and flame. Open valve slowly. Store and use with adequate ventilation. Use with equipment rated for cylinder pressure and cleaned for oxygen service. Cylinder temperature should not exceed 125°F (52°C). Close valve when not in use; keep closed even when empty. Always secure cylinder. Install cap, if provided, when not in use. Use a backflow prevention device in any piping. Use per MSDS provided and Praxair safety practices booklets P-3499 and P-14-153; obtain from your local supplier.

RX ONLY

WARNING! Administration this gas mixture may be hazardous or contraindicated. For use only by or under the supervision of a licensed

practitioner who is experienced in the use and administration of gas mixtures and is familiar with the indications, effects, dosages, methods, and

frequency and duration of administration, and with the hazards, contraindications, and side effects and the precautions to be taken.

IN CASE OF EMERGENCY: CALL 1-800-645-4633

Copyright 1997-1998, 2003, 2007 Praxair Technology, Inc.

DO NOT REMOVE THIS LABEL

Praxair, the flowing airstream design and Medipure are trademarks of Praxair Technology, Inc. DISTRIBUTED BY PRAXAIR, INC, DANBURY, CT 06810-5113